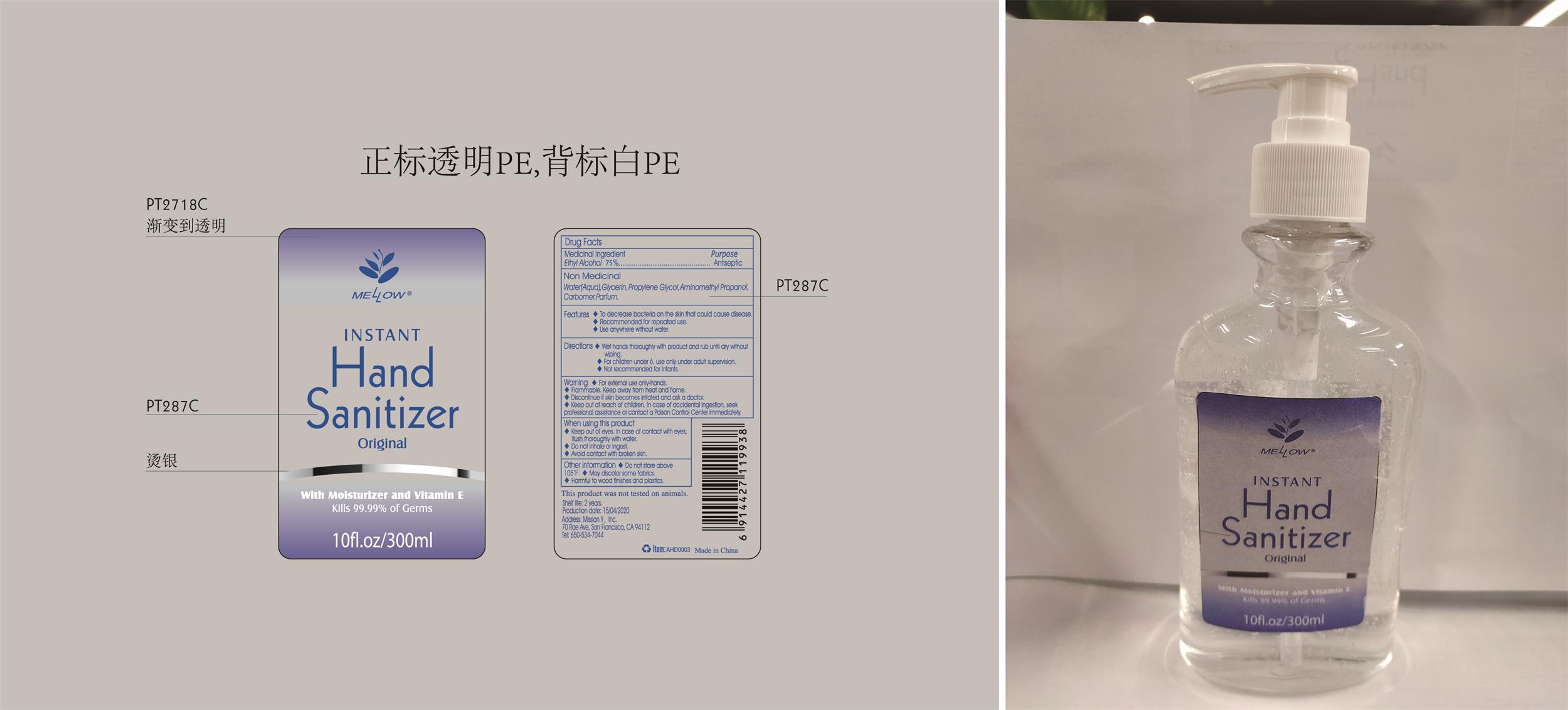 DRUG LABEL: Mellow 300ml hand sanitizer original
NDC: 54860-390 | Form: LIQUID
Manufacturer: Shenzhen Lantern Scicence Co.,Ltd.
Category: otc | Type: HUMAN OTC DRUG LABEL
Date: 20220410

ACTIVE INGREDIENTS: ALCOHOL 75 mL/100 mL
INACTIVE INGREDIENTS: PROPYLENE GLYCOL 0.01 mL/100 mL; LEMON 0.1 mL/100 mL; CARBOMER 940 0.35 mL/100 mL; AMINOMETHYLPROPANOL 0.11 mL/100 mL; WATER 28.42 mL/100 mL; GLYCERIN 0.01 mL/100 mL

Mellow 300ml hand sanitizer original

Medicical Ingredient

Medicical Ingredient Purpose

Ethyl Alcohol 75%（V/V） Antiseptic

Features

To decrease bacteria on the skin that could cause disease.

Recommended for repeated use.

Use anywhere without water.

DOSAGE AND ADMINISTRATION

Recommended for repeated use.

use anywhere without water.

Warning

For external use only-hands.

Flammable,keep away from heat and flame.

Discontinue if skin becomes irritated and ask a doctor.

Keep out of reach of children. In case of accidental ingestion,seek professional assistance or contact a Poison Control Center immediately.

WARNINGS AND PRECAUTIONS

For external use only.

Flammable, keep away from heat and flame.

STOP USE

Discontinue if skin becomes irritated and ask a doctor .

Keep out of reach of children. In case of accidental ingestion, seek professional assistance or contact a poson control center immediately.

Non-Medicinal

Water, Glycerin,Propylene Glycol,Carbomer,,Aminomethyl propanol,Parfum.

Directions

Wet hands thoroughly with product and rub until dry without wiping

For children under 6, use only under adult supervision.

Not recommended for infants.

When using this product

keep out of eyes. In case of contact with eyes, flush thoroughly with water.

Do not inhale or ingest.

Avoid contact with broken skin.

Other information

Do not store above 105F.

May discolor some fabrics.

Harmful to wood finishes and plastics.

When using this product

keep out of eyes,In case of contact with eyes,flush thoroughly with water

Do not inhale or ingest

Avoid contact with broken skin.

other information

Do not store above 105℉

May discolor some fabrics.

Harmful to wood finishes and plastics。